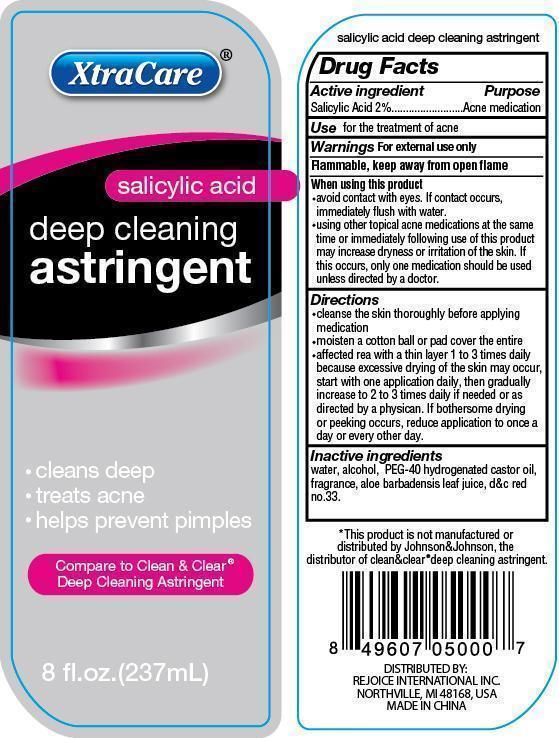 DRUG LABEL: XtraCare Deep Cleaning Astringent
NDC: 57337-035 | Form: GEL
Manufacturer: Rejoice International
Category: otc | Type: HUMAN OTC DRUG LABEL
Date: 20240228

ACTIVE INGREDIENTS: SALICYLIC ACID 5 mg/237 mg
INACTIVE INGREDIENTS: WATER; ALCOHOL; POLYOXYL 40 CASTOR OIL; ALOE VERA LEAF; D&C RED NO. 33

XtraCare Deep Cleaning Astringent

Active Ingredient Purpose

Salicylic Acid 2% ................ Acne Medication

PURPOSE

XtraCare (salicylic acid) deep cleaning astringent

- cleans deep
- treats acne
- helps prevent pimples

Compare to Clean & Clear® Deep Cleaning Astringent

8 fl. oz. (237 mL)

salicylic acid deep cleaning astringent

keep out of reach of children

INDICATIONS AND USAGE

Use for the treatment of acne

Warnings For external use only

Flammable, keep away from open flame

When using this product

- avoid contact with eyes. If contact occurs, immediately flush with water.
- using other topical acne medications at the same time or immediately following use of this product may increase dryness or irritation of the skin. If this occurs, only one medication should be used unless directed by a doctor.

Directions

- cleanse the skin thoroughly before applying medication
- moisten a cotton ball or pad cover the entire
- affected rea with a thin layer 1 to 3 times daily because excessive drying of the skin may occur, start with one application daily, then gradually increase to 2 to 3 times daily if needed or as directed by a physician. If bothersome drying or peeking occurs, reduce application to once a day or every other day.

Inactive Ingredients

water, alcohol, PEG-40 hydrogenated castor oil, fragrance, aloe barbadensis leaf juice, d&c red no.33

OTHER SAFETY INFORMATION

*This product is not manufactured or distributed by Johnson&Johnson, the distributor of clean&clear®deep cleansing astringent.

DISTRIBUTED BY:

REJOICE INTERNATIONAL INC.

NORTHVILLE, MI 48168 USA

MADE IN CHINA